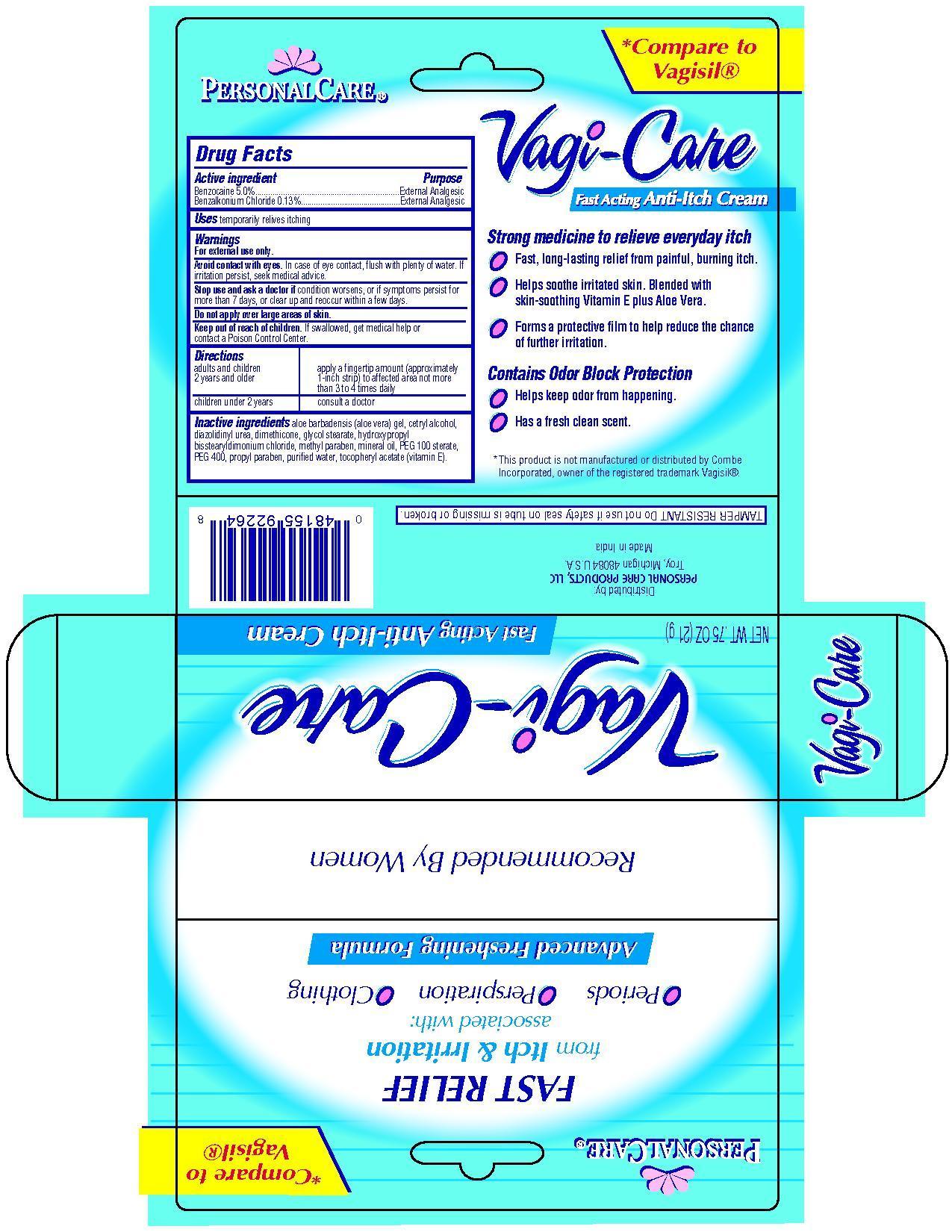 DRUG LABEL: Vagi care
NDC: 29500-2264 | Form: CREAM
Manufacturer: Personal Care Products
Category: otc | Type: HUMAN OTC DRUG LABEL
Date: 20200725

ACTIVE INGREDIENTS: BENZOCAINE 1.05 g/21 g; BENZALKONIUM CHLORIDE 0.003 g/21 g
INACTIVE INGREDIENTS: ALOE VERA LEAF; CETYL ALCOHOL; DIAZOLIDINYL UREA; DIMETHICONE; GLYCOL STEARATE; HYDROXYPROPYL BISSTEARYLDIMONIUM CHLORIDE; METHYLPARABEN; MINERAL OIL; PEG-100 STEARATE; POLYETHYLENE GLYCOL 400; PROPYLPARABEN; WATER; .ALPHA.-TOCOPHEROL

Vagi Care

For external use only.

Avoid contact with eyes. In case of eye contact, flush with plenty of water. If irritation persist, seek medical advice.

Stop use and ask a doctor if conditin worsens, or if symptoms persist for more than 7 days or clear up and reoccur within a few days.

Do not apply over large areas of skin.

Active Ingredient

Benzocaine 5.0%

Benzalkonium Chloride 0.13%

warnings

For external use only.

Avoid contact with eyes. In case of eye contact flush with plenty of water. If irritation persist, seek medical advice.

Stop use and ask a doctor if condition worsens, or if symptoms persist for more than 7 days, or clear up and reoccur within a few days.

Do not apply over large areas of skin.

DOSAGE AND ADMINISTRATION

Directions adults and children 2 years and older-Apply fingertip amount (approximately 1-inch strip) to affected area not more than 3 to 4 times daily

children under 2 years-consult a doctor

Keep out of reach of children. If swallowed, get medical help or contact a Poison Control Center.

INDICATIONS AND USAGE

Uses temporarily relieves itching

Purpose External Analgesic

INACTIVE INGREDIENT

Aloe Barbadensis (aloe vera) gel, cetryl alcohol, diazolidinyl urea, dimethicone, glycol stearate, hydroxypropyl bisstearyldimonium chloride, methyl paraben, mineral oil, PEG 100 stearate, PEG 400, propyl paraben, prified water, tocopheryl acetate (vitamin e)